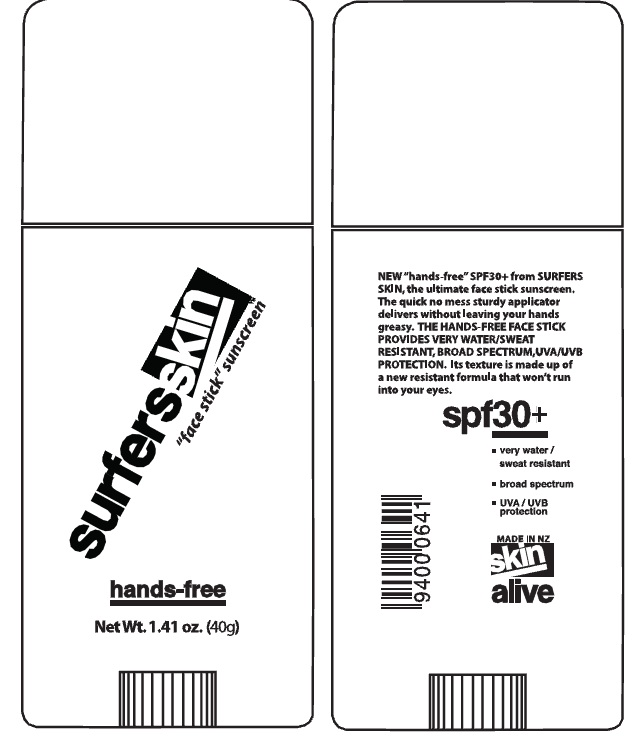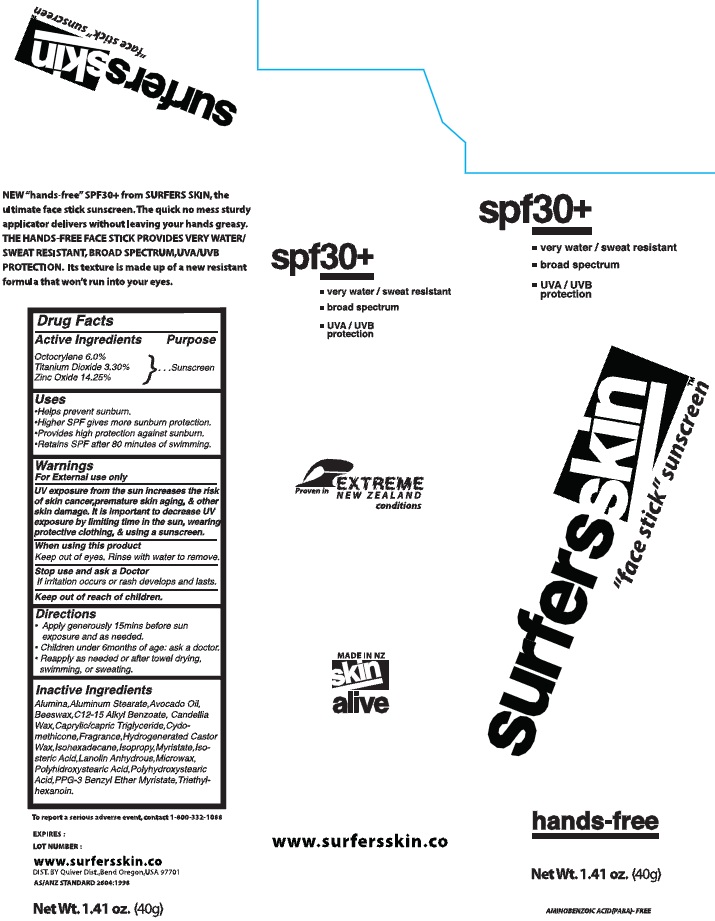 DRUG LABEL: SurfersSkin Face Sunscreen
NDC: 75916-3025 | Form: STICK
Manufacturer: Skin Alive, Ltd.
Category: otc | Type: HUMAN OTC DRUG LABEL
Date: 20110203

ACTIVE INGREDIENTS: OCTOCRYLENE 6 g/100 g; TITANIUM DIOXIDE 3.3 g/100 g; ZINC OXIDE 14.25 g/100 g
INACTIVE INGREDIENTS: ALUMINUM OXIDE; ALUMINUM STEARATE; AVOCADO OIL; YELLOW WAX; ALKYL (C12-15) BENZOATE; CANDELILLA WAX; MEDIUM-CHAIN TRIGLYCERIDES; CYCLOMETHICONE; HYDROGENATED CASTOR OIL; ISOHEXADECANE; ISOPROPYL MYRISTATE; ISOSTEARIC ACID; LANOLIN; MICROCRYSTALLINE WAX; HYDROXYSTEARIC ACID; TRIETHYLHEXANOIN

SurfersSkin "Face Stick" Sunscreen

Active Ingredients

Octocrylene 6.0%

Titanium Dioxide 3.30%

Zinc Oxide 14.25%

Purpose

Sunscreen

Uses

Helps prevent sunburn

Higher SPF gives more sunburn protection

Provides high protection against sunburn

Regains SPF after 80 minutes of sweating.

Warnings

For external use only

UV exposure from the sun increases the risk of skin cancer, premature skin aging and other skin damage. It is important to decrease UV exposure by limiting time in the sun, wearing protective clothing and using a sunscreen.

When using this product

Keep out of eyes. Rinse with water to remove.

Stop use and ask a doctor

if irritation occurs or rash develops ad lasts.

Directions

apply generously 15mins before sun exposure and as needed

Children under 6 months of age: ask a doctor.

Reapply as needed or after towel drying, swimming or sweating.

Inactive Ingredients

Alumina, Aluminum Stearate, Avocado Oil, Beeswax, C12-15 Alkyl Bezoate, Candellia Wax, Capryllic/capric Triglyceride, Cydomethicone, Fragrance, Hydrogenerated Castor Wax, Isohexadecane, Isopropyl Myristate, Isosteric Acid, Lanolin Anhydrous, Microwax, Polyhidroxystearic Acid, Polyhydroxystearic Acid, PPG-3 Benzyl Ether Myristate, Triethylhexanoin.

DESCRIPTION

New "hands-free" SPF 30+ from SURFERS SKIN, the ultimate face stick sunscreen. The quick no mess sturdy applicator delivers without leaving your hands greasy. THE HANDS-FREE FACE STICK PROVIDES VERY WATER/SWEAT RESISTANT, BROAD SPECTRUM UVA/UVB PROTECTION. Its texture is made up of a new resistant formula that won't run into your eyes.

To report a serious adverse event, contact 1-800-332-1088

Expires:

Lot Number:

ww.snowskin.co

DIST. BY Quiver Dist, Bend Oregon, USA 97701

AS/ANZ STANDARD 2604-1998

Net Wt. 1.41oz (40g)

PACKAGE LABEL

SPF 30+

very water / sweat resistant

broad spectrum

UVA/UVB protection

Proven in extreme new zealand conditions

SurfersSkin "face stick" sunscreen

hands free

Net Wt. 1.41 oz (40g)

aminobenzoic acid (PABA)-free